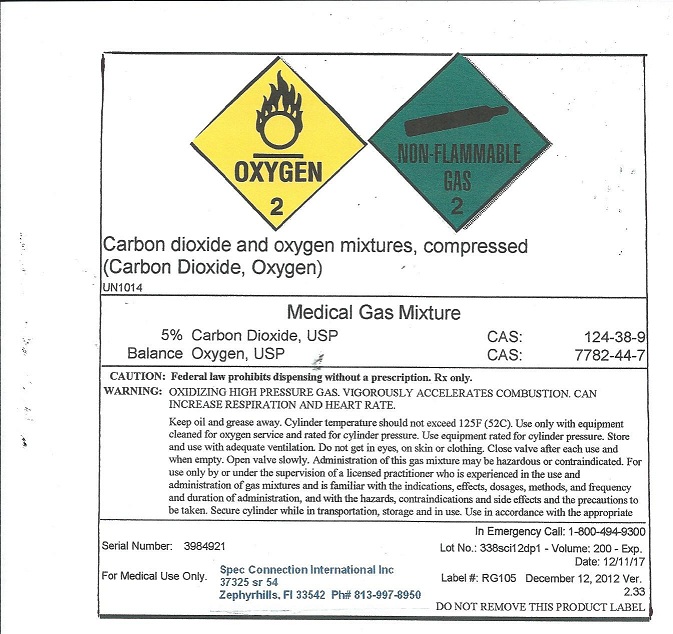 DRUG LABEL: Carbon Dioxide Oxygen Mixture
NDC: 54776-003 | Form: GAS
Manufacturer: Spec Connection International Inc
Category: prescription | Type: HUMAN PRESCRIPTION DRUG LABEL
Date: 20121229

ACTIVE INGREDIENTS: Carbon Dioxide 200 mL/1 L; Oxygen 800 mL/1 L

Carbon Dioxide Oxygen Mixture

PACKAGE LABEL

OXYGEN 2 NON-FLAMMABLE GAS 2 Carbon dioxide and oxygen mixtures, compressed (Carbon Dioxide, Oxygen) UN1014 Medical Gas Mixture 5% Carbon Dioxide, USP CAS: 124-38-9 Balance Oxygen, USP CAS: 7782-44-7 CAUTION: Federal law prohibits dispensing without a prescription. Rx Only. WARNING: OXIDIZING HIGH PRESSURE GAS. VIGOROUSLY ACCELERATES COMBUSTION. CAN INCREASE RESPIRATION AND HEART RATE. Cylinder temperature should not exceed 125 degrees F (52 degrees C). Use only with equipment cleaned for oxygen service and rated for cylinder pressure. Use equipment rated for cylinde pressure. Store and use with adequate ventilation. Do not get in eyes, on skin or clothing. Close valve after each use and when empty. Open valve slowly. Administration of this gas mixture may be hazardous or contraindicated. For use only by or under the supervision of a licensed practitioner who is experienced in the use and administration of gas mixtures and is familiar with the indications, effects, dosages, methods, and frequency and duration of administration, and with the hazards, contraindications and side effects and the precautions to be taken. Secure cylinder while in transportation, storage, and in use. Use in accordance with the appropriate Serial Number: 3984921 In Emergency Call: 1-800-494-9300 Lot No: 338sci12dp1 Volume 200 Exp Date: 12/11/17 Label #: RG105 December 12, 2012 Ver 2.33 For Medical Use Only. Spec Connection International Inc 37325 sr 54 Zephyrhills, FL 33542 Ph# 813-997-8950 DO NOT REMOVE THIS PRODUCT LABEL.